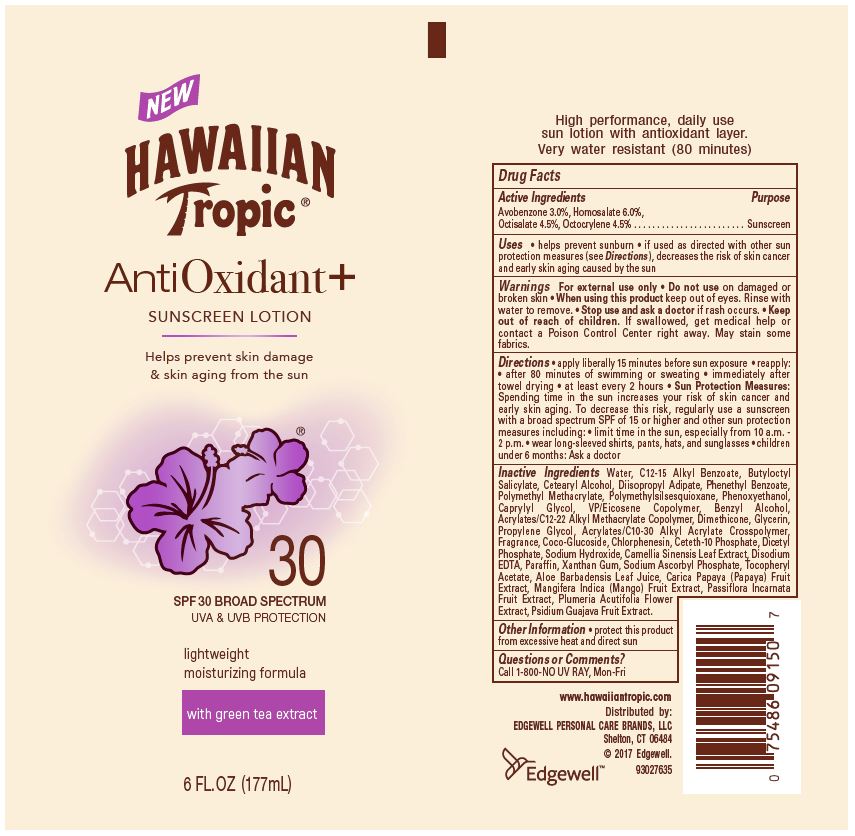 DRUG LABEL: Hawaiian Tropic
NDC: 63354-927 | Form: LOTION
Manufacturer: Edgewell Personal Care Brands LLC
Category: otc | Type: HUMAN OTC DRUG LABEL
Date: 20241031

ACTIVE INGREDIENTS: OCTOCRYLENE 4.5 g/100 g; AVOBENZONE 3 g/100 g; OCTISALATE 4.5 g/100 g; HOMOSALATE 6 g/100 g
INACTIVE INGREDIENTS: PARAFFIN; XANTHAN GUM; ALOE VERA LEAF; VINYLPYRROLIDONE/EICOSENE COPOLYMER; WATER; PROPYLENE GLYCOL; CARICA PAPAYA WHOLE; PLUMERIA RUBRA FLOWER; CETETH-10 PHOSPHATE; DIISOPROPYL ADIPATE; PHENETHYL BENZOATE; PHENOXYETHANOL; CAPRYLYL GLYCOL; ALKYL (C12-15) BENZOATE; BUTYLOCTYL SALICYLATE; CETOSTEARYL ALCOHOL; CHLORPHENESIN; SODIUM HYDROXIDE; EDETATE DISODIUM; .ALPHA.-TOCOPHEROL ACETATE; SODIUM ASCORBYL PHOSPHATE; CARBOMER INTERPOLYMER TYPE A (ALLYL SUCROSE CROSSLINKED); PASSIFLORA INCARNATA FLOWER; POLYMETHYLSILSESQUIOXANE (11 MICRONS); DIMETHICONE; GLYCERIN; BENZYL ALCOHOL; COCO GLUCOSIDE; POLY(METHYL METHACRYLATE; 450000 MW); GUAVA; MANGO; GREEN TEA LEAF; DIHEXADECYL PHOSPHATE

Active Ingredients

Avobenzone 3%, Homosalate 6%, Octisalate 4.5%, Octocrylene 4.5%

Purpose

Sunscreen

Uses

Helps prevent sunburn

If used as directed with other sun protection measures (see Directions), decreases the risk of skin cancer and early skin aging caused by the sun

Warnings

For external use only

Do not use

on damaged or broken skin

When using this product

Keep out of eyes. Rinse with water to remove.

Stop use and ask a doctor

if rash occurs.

Keep out of reach of children

If swallowed, get medical help or contact a Poison Control Center right away.

May stain

some fabrics.

Directions

Apply liberally 15 minutes before sun exposure. Reapply: after 80 minutes of swimming or sweating. Immediately after towel drying. At least every 2 hours. Sun Protection Measures: Spending time in the sun increases your risk of skin cancer and early skin aging. To decrease this risk, regularly use a sunscreen with a broad spectrum SPF of 15 or higher and other sun protection measures including: Limit time in the sun, especially from 10 a.m. - 2 p.m. Wear long-sleeved shirts, pants, hats, and sunglasses. Children under 6 months: Ask a doctor.

Inactive Ingredients

Water, C12-15 Alkyl Benzoate, Butyloctyl Salicylate, Cetearyl Alcohol, Diisopropyl Adipate, Phenethyl Benzoate, Polymethyl Methacrylate, Polymethylsilsesquioxane, Phenoxyethanol, Caprylyl Glycol, VP/Eicosene Copolymer, Benzyl Alcohol, Acrylates/C12-22 Alkyl Methacrylate Copolymer, Dimethicone, Glycerin, Propylene Glycol, Acrylates/C10-30 Alkyl Acrylate Crosspolymer, Fragrance, Coco-Glucoside, Chlorphenesin, Ceteth-10 Phosphate, Dicetyl Phosphate, Sodium Hydroxide, Camellia Sinensis Leaf Extract, Disodium EDTA, Paraffin, Xanthan Gum, Sodium Ascorbyl Phosphate, Tocopheryl Acetate, Aloe Barbadensis Leaf Juice, Carica Papaya (Papaya) Fruit Extract, Mangifera Indica (Mango) Fruit Extract, Passiflora Incarnata Fruit Extract, Plumeria Acutifolia Flower
Extract, Psidium Guajava Fruit Extract.

Other Infromation

protect this product from excessive heat and direct sun

Questions or Comments?

Call 1-800-NO UV RAY, Mon-Fri

PACKAGE LABEL

HAWAIIAN

Tropic(R)

AntiOxidant+

SUNSCREEN LOTION

Helps prevent skin damage

& skin aging from the sun

30

SPF 30 BROAD SPECTRUM

UVA & UVB PROTECTION

light weight

moisturizing formula

with green tea extract

6 FL. OZ (177 mL)